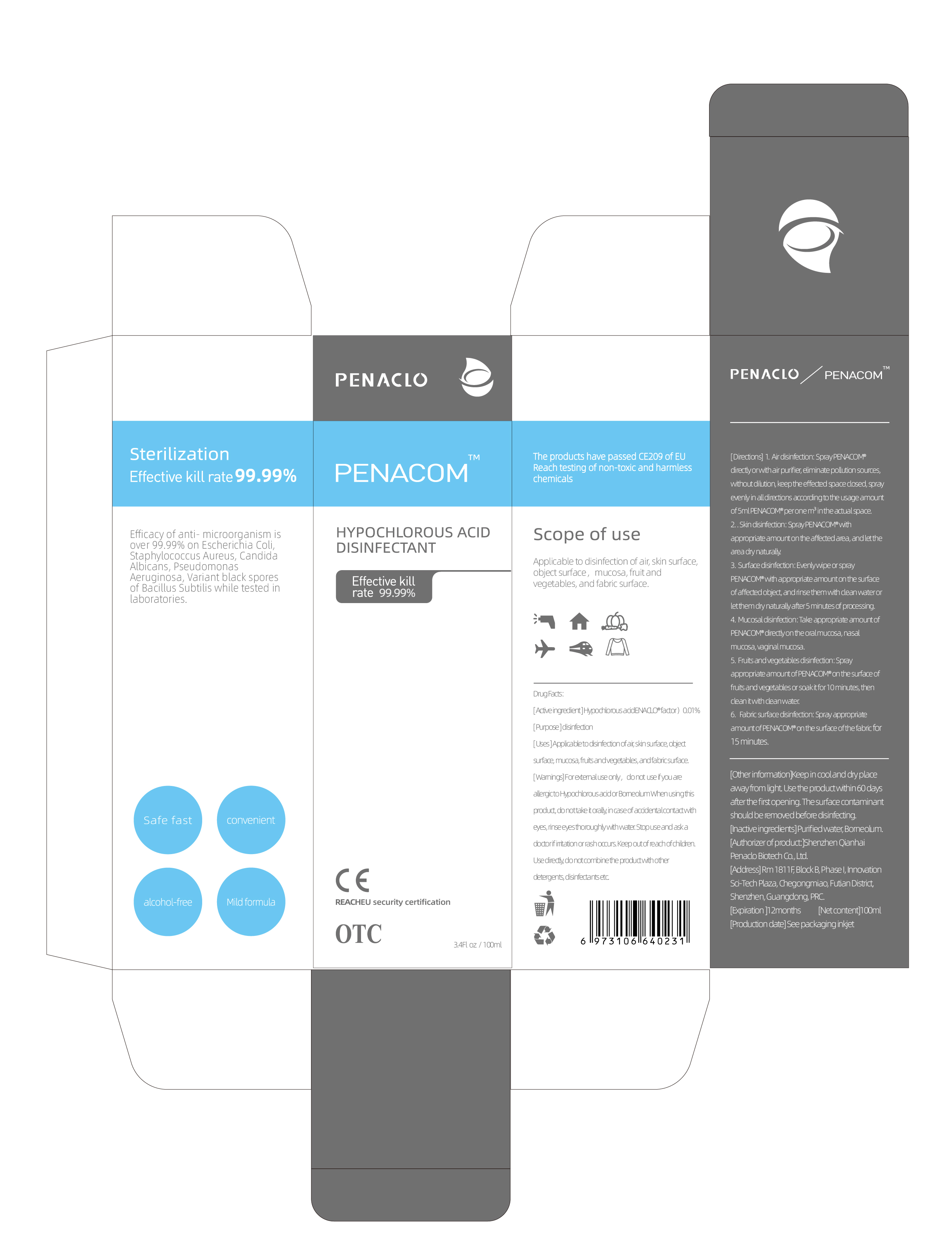 DRUG LABEL: PENACOM Hypochlorous acid disinfectant
NDC: 81763-001 | Form: SPRAY
Manufacturer: Shenzhen Qianhai PENACLO Biotechnology Co., Ltd
Category: otc | Type: HUMAN OTC DRUG LABEL
Date: 20210401

ACTIVE INGREDIENTS: HYPOCHLOROUS ACID 0.01 g/100 mL
INACTIVE INGREDIENTS: BORNEOL; WATER

81763-001
PENACOM Hypochlorous acid disinfectant

Active Ingredient(s)

Hypochlorous acid ENACLO factor) 0.01%

Purpose

disinfection

Use

Applicable to disinfection of air, skin surface, object surface, mucosa, fruit and vegetables, and fabric surface.

Warnings

For extermal use only, do not use of you are alergic to Hypochlorous acid or Borneolum

When using this produc, do not take toraly, in case of acidental contact with eyes, rinse eyes thoroughy with water

Stop use and ask a doctor if it at on or rash occurs. Keep out of reach of children.
Use diecty, do not combine the product wth other detergents, disinfectants etc.

Do not use

For extermal use only, do not use of you are alergic to Hypochlorous acid or Borneolum

When using this produc, do not take toraly, in case of acidental contact with eyes, rinse eyes thoroughy with water

Use diecty, do not combine the product wth other detergents, disinfectants etc.

WHEN USING

When using this produc, do not take toraly, in case of acidental contact with eyes, rinse eyes thoroughy with water

Stop use and ask a doctor if it at on or rash occurs. Keep out of reach of children.
Use diecty, do not combine the product wth other detergents, disinfectants etc.

Stop use and ask a doctor if it at on or rash occurs.
Keep out of reach of children.

Keep out of reach of children.
Use diecty, do not combine the product wth other detergents, disinfectants etc.

Directions

1.Ardisinfection:Spray PENACOM direct yorwthairpurfier eliminate polution sources, without dition, keep the effected space closed, spray evenly in all directions according to the usage amount of 5ml PENACOM peronemin the actual space.
2.Skindsifecion:Spray PENACOM with appropriate amount on the affected area, and let the area dry naturaly.
3.Surface disinfect on:Evenly wipe or spray PENACOM with appropriate amount on the surface of affected object, and rinse them with dean water or let the m dry natura y after 5 minutes of processing.
4.Mucosal dsn fect on:Take appropriate amount of PENACOM dre cty on the oral mucosa, nasal mucosa, vaginal mucosa.
5.Fruts and vegetables diifeci on:Spray appropriate amount of PENA COM on the surface of fruits and vegetables or soakt for 10 minutes, then clean it with clean water
6.Fabric surface dsn fection:Spray appropriate amount of PENACOM on the surface of the fabrc for 15 minutes.

Other information

Keep in cool and dy place away from ght Use the product with in 60 days after the first opening.The surface contaminant should be removed before dsinfecing.

Inactive ingredients

Purified water, Borneolum.

Package Label - Principal Display Panel

LABEL81763-001-01 100ml